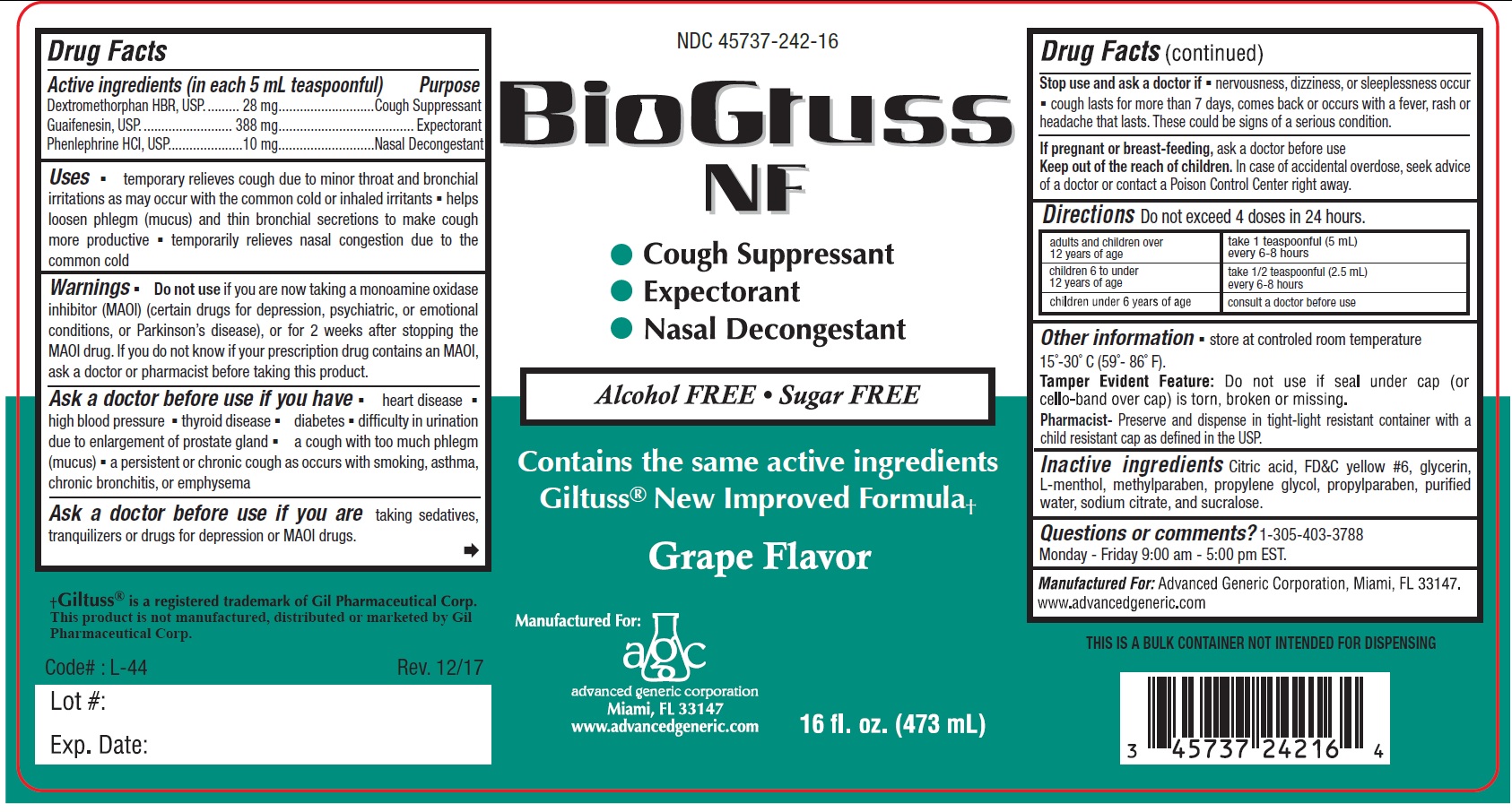 DRUG LABEL: BioGtuss
NDC: 45737-242 | Form: LIQUID
Manufacturer: Advanced Generic Corporation
Category: otc | Type: HUMAN OTC DRUG LABEL
Date: 20241220

ACTIVE INGREDIENTS: DEXTROMETHORPHAN HYDROBROMIDE 28 mg/5 mL; GUAIFENESIN 388 mg/5 mL; PHENYLEPHRINE HYDROCHLORIDE 10 mg/5 mL
INACTIVE INGREDIENTS: FD&C YELLOW NO. 6; GLYCERIN; MENTHOL; METHYLPARABEN; PROPYLENE GLYCOL; PROPYLPARABEN; WATER; SODIUM CITRATE; SUCRALOSE

AGC- BioGTussNF 242

Active Ingredients: (in each 5 mL tsp.) Purpose

Dextromethorphan HBr 28 mg.................. Cough Suppressant

Guaifenesin 388 mg .............................................. Expectorant

Phenylephrine HCl 10 mg...........................Nasal Decongestant

Purpose

Cough suppressant

Expectorant

Nasal Decongestant

Uses

- temporary relieves cough due to minor throat and bonchial irritations as may occur with the common cold or inhaled irritants
- helps loosen phlegm (mucus) and thin bronchial secretaions to make cough more productive
- temporarily relieves nasal congestion due to the common cold.

Warnings

Do not use If you are now taking a prescription monoamine oxidase inhibitor (MAOI) (certain drugs for depression, psychiatric or emotional conditions or Parkinson’s disease), or for 2 weeks after stopping the MAOI drug. If you do not know if you are taking a prescription drug that contains an MAOI; ask your doctor or pharmacist before taking this product.

Ask a doctor before use if you have

- heart disease
- high blood pressure
- thyroid disease
- diabetes
- difficulty in urination due to enlargement of prostate gland
- a cough with too much phlegm (mucus)
- a persistent or chronic cough as occurs with smoking, asthma, chronic bronchitis, or emphysema

Ask a doctor before use if you are taking sedatives, tranquilizers or drugs for depression or MAOI drugs.

Stop use and ask a doctor if

- nervousness, dizziness, or sleeplessness occur
- cough lasts for more than 7 days, comes back or occurs with a fever, rash or headache that lasts. These could be signs of a serious condition

Keep out of reach of children.In case of accidental overdose, seek advice or a doctor or contact a Poison Control Center right away.

PREGNANCY OR BREAST FEEDING

If pregnant or breast-feeding,ask a doctor before use.

DOSAGE AND ADMINISTRATION

DirectionsDo not exceed 6 doses in 24 hours.

adults and children over 12 years of age | take 1 teaspoonful (5 mL) every 6-8 hours
children 6 to under 12 years of age | take 1/2 teaspoonful (2.5 mL) every 6-8 hours
children under 6 years of age | consult a doctor before use

INACTIVE INGREDIENT

Inactive Ingredients citric acid, FDandC yellow No 6, glycerin, menthol, methylparaben, propylene glycol, propylparaben, purified water, sodium citrate and sucralose

Questions or comments?1-305-403-3788

Monday - Friday 9:00AM - 5:00 PM EST.

Manufactured For:Advanced Generic Corporation, Miami, Fl 33147

www.advancedgeneric.com